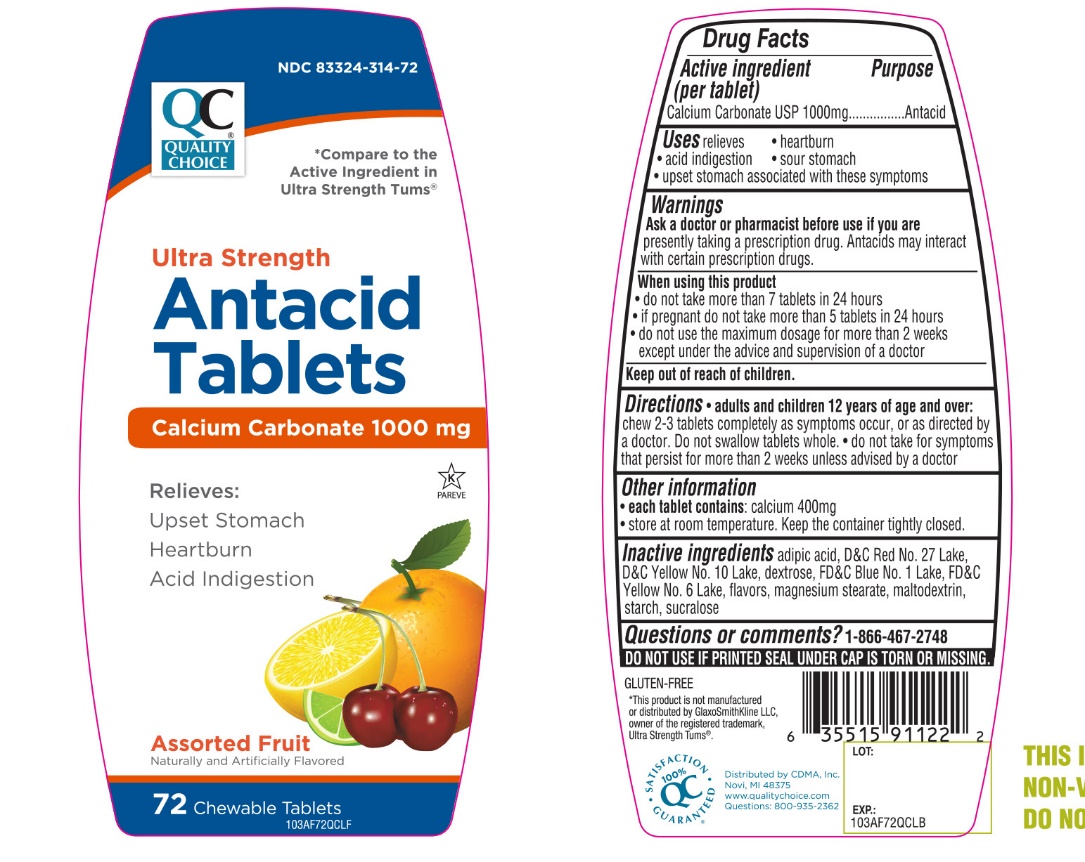 DRUG LABEL: Quality Choice

NDC: 83324-314 | Form: TABLET, CHEWABLE
Manufacturer: QUALITY CHOICE (Chain drug Marketing Assoiciation)
Category: otc | Type: HUMAN OTC DRUG LABEL
Date: 20251204

ACTIVE INGREDIENTS: CALCIUM CARBONATE 1000 mg/1 1
INACTIVE INGREDIENTS: ADIPIC ACID; FD&C BLUE NO. 1; DEXTROSE, UNSPECIFIED FORM; MAGNESIUM STEARATE; MALTODEXTRIN; D&C RED NO. 27; STARCH, CORN; SUCRALOSE; FD&C YELLOW NO. 6; D&C YELLOW NO. 10

Quality Choice Ultra Strength Antacid Calcium Carbonate 72 Chewable Tablets

Active ingredient (per tablet)

Calcium Carbonate USP 1000mg

Purpose

Antacid

Uses

relieves

- heartburn
- acid indigestion
- sour stomach
- upset stomach associated with these symptoms

Warnings

Ask a doctor or pharmacist before use if you arepresently taking a prescription drug. Antacids may interact with certain prescription drugs.

When using this product

- do not take more than 7 tablets in 24 hours
- if pregnant do not take more than 5 tablets in 24 hours
- do not use the maximum dosage for more than 2 weeks except under the advice and supervision of a doctor.

Directions

- adults and children 12 years of age and over: Chew 2-3 tablets completely as symptoms occur, or as directed by a doctor.
- Do not swallow tablets whole
- Do not take for symptoms that persist for more than 2 weeks unless advised by a doctor.

Other information

- each tablet contains: calcium 400 mg
- Store at room temperature. Keep the container tightly closed.

SAFETY SEALED: DO NOT USE IF PRINTED SEAL UNDER CAP IS TORN OR MISSING.

Inactive ingredients

adipic acid, D&C Red No. 27 Lake, D&C Yellow No. 10 Lake, dextrose, FD&C Blue No. 1 Lake, flavors, FD&C Yellow No. 6 Lake, magnesium stearate, maltodextrin, starch, sucralose,

Questions or comments?

1-866-467-2748

Package/Label Principal Display Panel

* Compare to the active ingredient in Ultra Strength Tums®

NDC 83324-314-72

QUALITY CHOICE

Ultra Strength

Antacid Tablets

Calcium Carbonate 1000 mg

Relieves:

Upset Stomach

Heartburn

Acid Indigestion

Assorted Fruit

72 Chewable Tablets

K PAREVE

GLUTEN- FREE

QC SATISFACTION GURANTEED

Distributed by C.D.M.A., Inc.

Novi, MI 48375

www.qualitychoice.com

Questions: 800-935-2362

*This product is not manufactured or distributed by GlaxoSmithKline LLC, owner of the registered trademark, Ultra Strength Tums®.